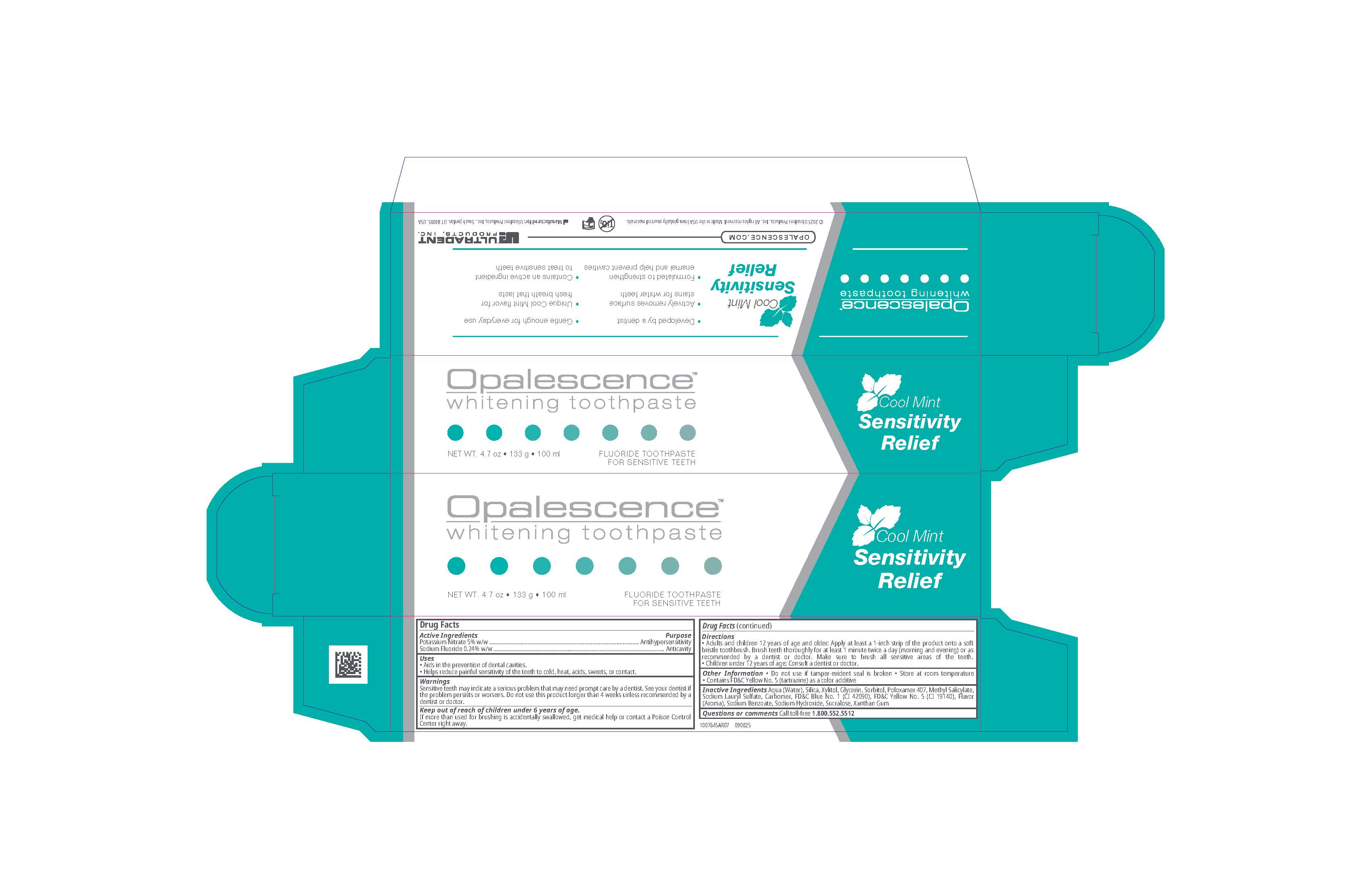 DRUG LABEL: Opalescence Whitening Sensitivity Relief
NDC: 51206-315 | Form: GEL, DENTIFRICE
Manufacturer: Ultradent Products, Inc.
Category: otc | Type: HUMAN OTC DRUG LABEL
Date: 20251201

ACTIVE INGREDIENTS: POTASSIUM NITRATE 50 mg/1 g; SODIUM FLUORIDE 1.1 mg/1 g
INACTIVE INGREDIENTS: SILICON DIOXIDE; SUCRALOSE; CARBOMER; SODIUM LAURYL SULFATE; POLOXAMER 407; FD&C YELLOW NO. 5; SORBITOL; METHYL SALICYLATE; XYLITOL; SODIUM BENZOATE; SODIUM HYDROXIDE; AQUA; XANTHAN GUM; GLYCERIN; FD&C BLUE NO. 1

Opalescence™ Whitening Toothpaste Sensitivity Relief

Drug Facts

Active Ingredients

Potassium Nitrate 5% w/w

Sodium Fluoride 0.24% w/w

Purpose

Antihypersensitivity

Anticavity

Uses

- Aids in the prevention of dental cavities
- Helps reduce painful sensitivity of the teeth to cold, heat, acids, sweets, or contact

Warnings

Sensitive teeth may indicate a serious problem that may need prompt care by a dentist. See your dentist if the problem persists or worsens. Do not use this product longer than 4 weeks unless recommended by a dentist or doctor

Keep out of reach of children under 6 years of age.

If more than used for brushing is accidentally swallowed, get medical help or contact a Poison Control Center right away

Directions

- Adults and children 12 years of age and older: Apply at least a 1-inch strip of the product onto a soft bristle toothbrush. Brush teeth thoroughly for at least 1 minute twice a day (morning and evening) or as recommended by a dentist or doctor. Make sure to brush all sensitive areas of the teeth.
- Children under 12 yeasrs of age: Consult a dentist or doctor.

Other Information

- Do not use if tamper-evident seal is broken
- Store at room temperature
- Contains FD&C Yellow No. 5 (tartrazine) as a color additive

Inactive Ingredients

Aqua (Water), Silica, Xylitol, Glycerin, Sorbitol, Poloxamer 407, Methyl Salicylate, Sodium Lauryl Sulfate, Carbomer, FD&C Blue No. 1 (CI 42090), FD&C Yellow No. 5 (CI 19140), Flavor (Aroma), Sodium Benzoate, Sodium Hydroxide, Sucralose, Xantham Gum

Questions or comments

Call toll-free 1.800.552.5512

Principal Display Panel - 4.7 oz Tube Carton

Opalescence Whitening Toothpaste

Sensitivity Relief

Cool Mint

NET WT. 4.7 oz * 133 g 8 100 ml

FLUORIDE TOOTHPASTE

FOR SENSITIVE TEETH